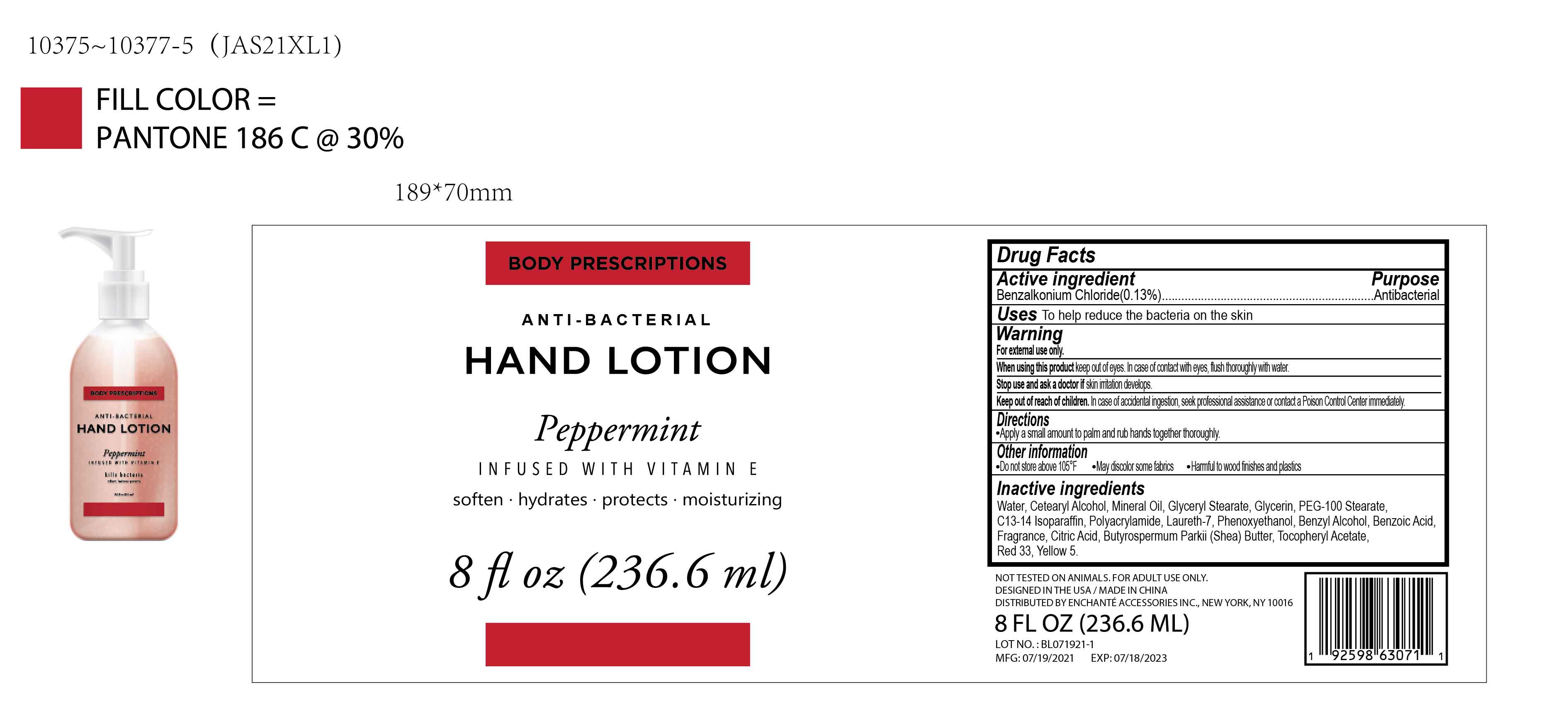 DRUG LABEL: BODY PRESCRIPTIONS INFUSED WITH VITAMIN E Peppermint ANTIBACTERIAL HAND
NDC: 50563-465 | Form: LOTION
Manufacturer: ENCHANTE ACCESSORIES INC.
Category: otc | Type: HUMAN OTC DRUG LABEL
Date: 20210704

ACTIVE INGREDIENTS: BENZALKONIUM CHLORIDE 0.13 g/100 mL
INACTIVE INGREDIENTS: MINERAL OIL; GLYCERYL STEARATE SE; PEG-100 STEARATE; C13-14 ISOPARAFFIN; GLYCERIN; WATER; POLYACRYLAMIDE (1500 MW); LAURETH-7; PHENOXYETHANOL; BENZYL ALCOHOL; BENZOIC ACID; CITRIC ACID MONOHYDRATE; BUTYROSPERMUM PARKII (SHEA) BUTTER UNSAPONIFIABLES; .ALPHA.-TOCOPHEROL ACETATE; D&C RED NO. 33; FD&C YELLOW NO. 5; CETOSTEARYL ALCOHOL

50563-465/JAS21XL1

Active Ingredient

Benzalkonium Chloride 0.13%

Purpose

Antibacterial

Use

■ To help reduce the bacteria on the skin

WARNINGS

For external use only

When using this product, keep out of eyes. In case of contact with eyes, flush thoroughly with water.

Stop use and ask a doctor if skin irritation develops.

Keep out of reach of children. In case of accidenta ingestion, seek professional assistance or contact a Poison Control Center immdiately.

Directions

Apply a small amount to palm and rub hands together thoroughly

Other Information

Do not store above 105F

May doscolor some fabrics

Harmful to wood finishes and plastics

Inactive ingredients

Water, Cetearyl Alcohol, Mineral Oil, Glyceryl Stearate, Glycerin, PEG-100 Stearate, C13-14 Isoparaffin, Polyacrylamide, Laureth-7, Phenoxyethanol, Benzyl Alcohol, Benzoic Acid, Fragrance (Parfum), Citric Acid, Butyrospermum Parkii (Shea) Butter, Tocopheryl Acetate, Red 33, Yellow 5